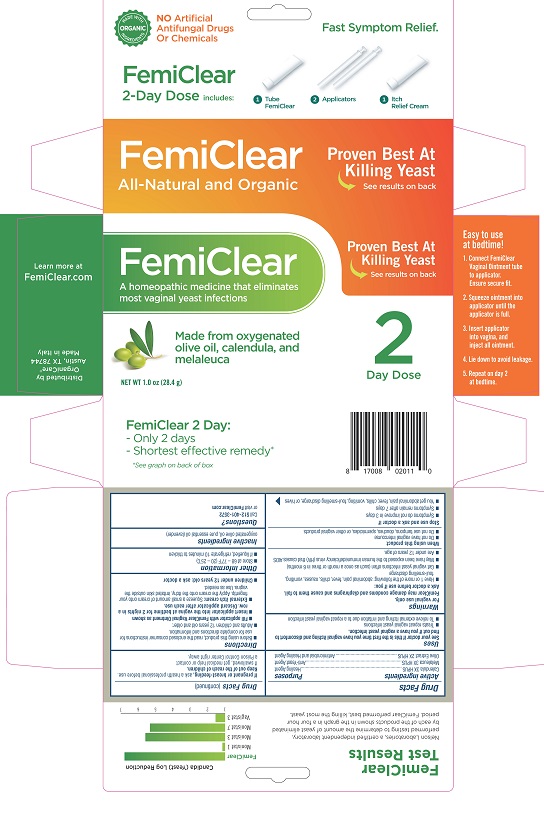 DRUG LABEL: FemiClear
NDC: 71042-005 | Form: OINTMENT
Manufacturer: OrganiCare Nature's Science, LLC
Category: homeopathic | Type: HUMAN OTC DRUG LABEL
Date: 20181002

ACTIVE INGREDIENTS: MELALEUCA CAJUPUTI LEAF OIL 3 [hp_X]/28 g; OLEA EUROPAEA FRUIT VOLATILE OIL 2 [hp_X]/28 g; CALENDULA OFFICINALIS FLOWERING TOP 3 [hp_X]/28 g
INACTIVE INGREDIENTS: LAVENDER OIL; OLIVE OIL

FEMICLEAR VAGINAL

Drug Facts

Active ingredients

Calendula 3X HPUS

Melaleuca 3X HPUS

Olive Extract 2X HPUS

Purposes

Healing Agent

Anti-Yeast Agent

Antimicrobial and Healing Agent

Uses

See your doctor if this is the first time you have vaginal itching and discomfort to find out if you have a vaginal yeast infection.

- Treats repeat vaginal yeast infections
- To relieve external itching and irritation due to a repeat vaginal yeast infection

Warnings

For vaginal use only.

FemiClear may damage condoms and diaphragms and cause them to fail.

Ask a doctor before use if you:

- Have 1 or more of the following: abdominal pain, fever, chills, nausea, vomiting, foul-smelling discharge
- Get vaginal yeast infections often (such as once a month or three in 6 months)
- May have been exposed to the human immunodeficiency virus (HIV) that causes AIDS
- Are under 12 years of age.

When using this product

- Do not have vaginal intercourse
- Do not use tampons, douches, spermicides, or other vaginal products

Stop use and ask a doctor if

- Symptoms do not improve in 3 days
- Symptoms remain after 7 days
- You get abdominal pain, fever, chills, vomiting, foul-smelling discharge, or hives

PREGNANCY OR BREAST FEEDING

If pregnant or breast-feeding, ask a health professional before use.

Keep out of reach of children. If swallowed, get medical help or contact a Poison Control Center right away.

Directions

- Before using this product, read the enclosed consumer instructions for use for complete directions and information.
- Adults and children 12 years old and older:
- Fill applicator with Femi-Clear Vaginal Ointment as shown
- Insert applicator into the vagina at bedtime for 2 nights in a row. Discard applicator after each use.
- External itch cream: Squeeze a small amount of cream onto your fingertip. Apply the cream onto the itchy, irritated skin outside the vagina. Use as needed.
- Children under 12 years old: ask a doctor

Other information

- store at 68° to 77°F (20° to 25°C)
- if liquefied, refrigerate 10 minutes to thicken

Inactive ingredients

oxygenated olive oil, pure essential oil (lavender)

Questions?

Call 512-401-3572 or

Visit FemiClear.com

Distributed by

OrganiCare®

Austin, TX 78744

Made in Italy

PACKAGE LABEL

MADE WITH ORGANIC INGREDIENTS

NO Artificial Antifungal Drugs or Chemicals

Fast Symptom Relief.

FemiClear

All-Natural and Organic

A homeopathic medicine that eliminates most vaginal yeast infections

Made from oxygenated olive oil, calendula and melaleuca

2 Day Dose

NET WT 1 oz (28.4 g)